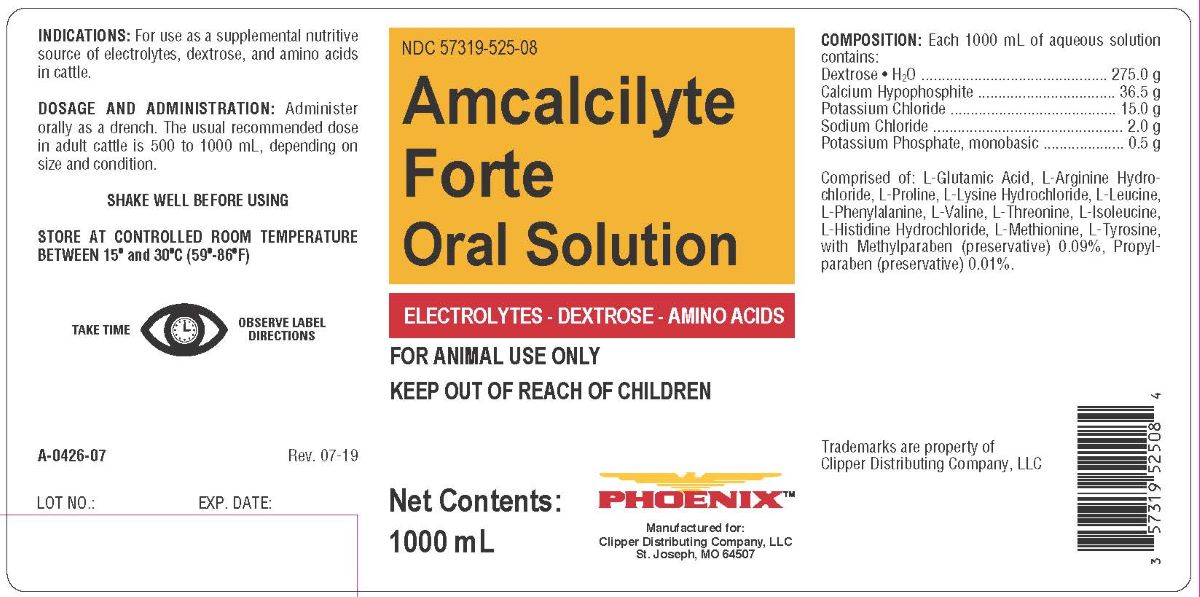 DRUG LABEL: AMCALCILYTE 
NDC: 57319-525 | Form: SOLUTION
Manufacturer: Clipper Distributing Company, LLC
Category: animal | Type: OTC ANIMAL DRUG LABEL
Date: 20240604

ACTIVE INGREDIENTS: CALCIUM HYPOPHOSPHITE 36.5 g/1000 mL; DEXTROSE MONOHYDRATE 275 g/1000 mL; POTASSIUM CHLORIDE 275 g/1000 mL; POTASSIUM PHOSPHATE, MONOBASIC 2 g/1000 mL; SODIUM CHLORIDE 0.5 g/1000 mL

AMCALCILYTE FORTE ORAL SOLUTION

INDICATIONS AND USAGE

Oral Solution

ELECTROLYTES - DEXTROSE - AMINO ACIDS

FOR ANIMAL USE ONLY

KEEP OUT OF REACH OF CHILDREN

INDICATIONS

For use as a supplemental nutritive source of electolytes, dextrose and amino acids in cattle.

DOSAGE AND ADMINISTRATION

Administer orally as a drench. The usual recommended dose in adult cattle is 500 to 1000 mL, depending on size and condition.

SHAKE WELL BEFORE USING

STORAGE AND HANDLING

STORE AT CONTROLLED ROOM TEMPERATURE
BETWEEN 15º and 30ºC (59º-86ºF)

TAKE TIME OBSERVE LABEL DIRECTIONS

COMPOSITION

Each 1000 mL of aqueous solution contains:

Dextrose • H2O ....................................... 275.0 g
Calcium Hypophosphite ............................ 36.5 g
Potassium Chloride .................................. 15.0 g
Sodium Chloride ........................................ 2.0 g
Potassium Phosphate, monobasic ............... 0.5 g

Comprised of: L-Glutamic Acid, L-Arginine Hydrochloride, L-Proline, L-Lysine Hydrochloride, L-Leuicne, L-Phenylalanine, L-Valine, L-Threonine, L-Isoleucine, L-Histidine Hydrochloride, L-Metionine, L-Tyrosine, with Methylparaben (preservative) 0.09%, Propylparaben (preservative)0.01%